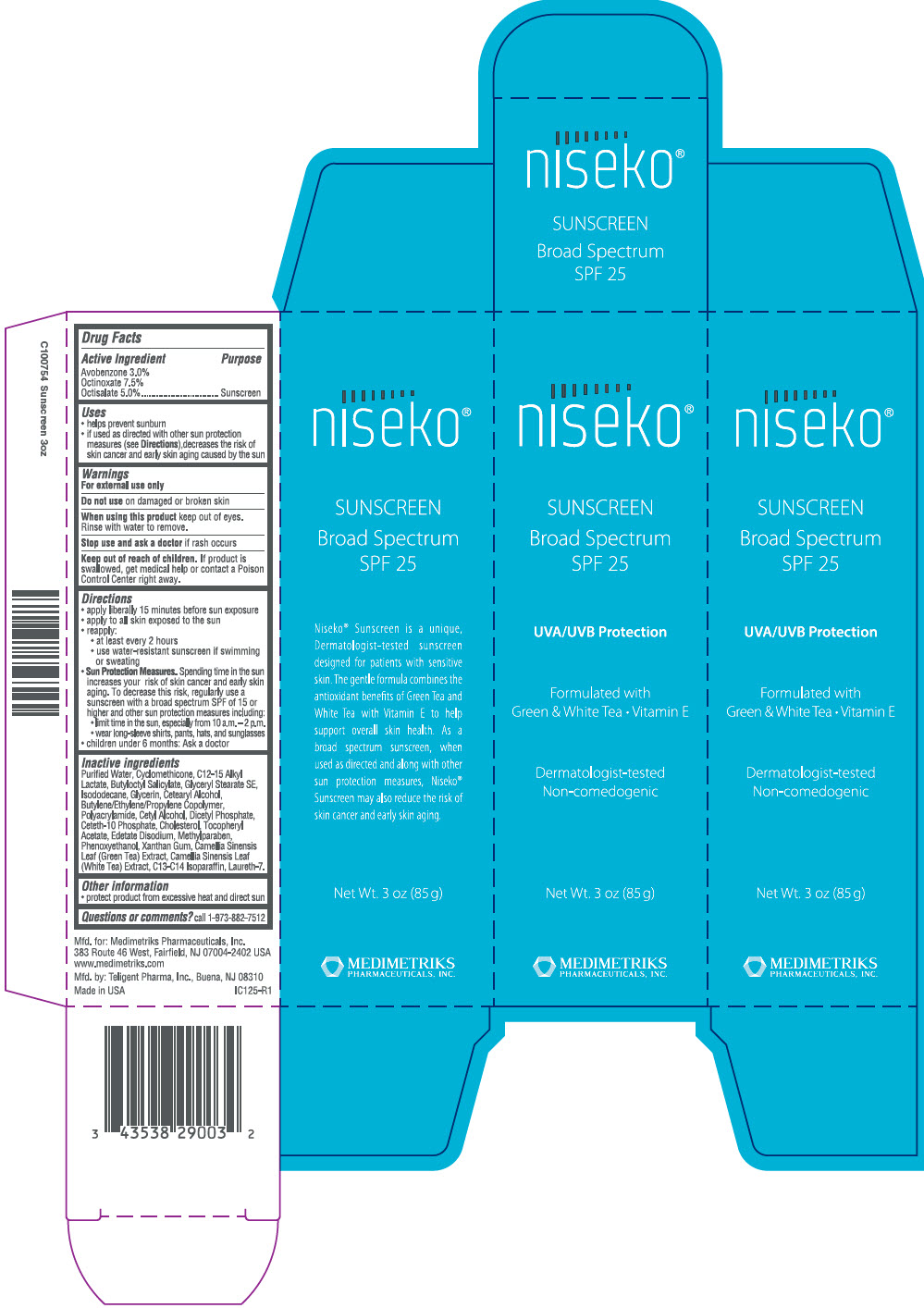 DRUG LABEL: Niseko Sunscreen SPF 25
NDC: 43538-290 | Form: CREAM
Manufacturer: Medimetriks Pharmaceuticals, Inc.
Category: otc | Type: HUMAN OTC DRUG LABEL
Date: 20181210

ACTIVE INGREDIENTS: Avobenzone 30 mg/1 g; Octinoxate 75 mg/1 g; Octisalate 50 mg/1 g
INACTIVE INGREDIENTS: water; C12-15 Alkyl lactate; butyloctyl salicylate; Glyceryl Stearate SE; isododecane; glycerin; cetostearyl alcohol; cetyl alcohol; dihexadecyl phosphate; ceteth-10 phosphate; cholesterol; .alpha.-tocopherol acetate; edetate disodium; methylparaben; phenoxyethanol; xanthan gum; green tea leaf; C13-14 isoparaffin; Laureth-7

Niseko™ Sunscreen SPF 25

Drug Facts

Active Ingredient

Avobenzone 3.0%
Octinoxate 7.5%
Octisalate 5.0%

Purpose

Sunscreen

Uses

- helps prevent sunburn
- if used as directed with other sun protection measures (see Directions),decreases the risk of skin cancer and early skin aging caused by the sun

Warnings

For external use only

Do not use on damaged or broken skin

When using this product keep out of eyes.

Rinse with water to remove.

Stop use and ask a doctor if rash occurs

Keep out of reach of children. If product is swallowed, get medical help or contact a Poison Control Center right away.

Directions

- apply liberally 15 minutes before sun exposure
- apply to all skin exposed to the sun
- reapply:
  - at least every 2 hours
  - use water-resistant sunscreen if swimming or sweating
- Sun Protection Measures. Spending time in the sun increases your risk of skin cancer and early skin aging. To decrease this risk, regularly use a sunscreen with a broad spectrum SPF of 15 or higher and other sun protection measures including:
  - limit time in the sun, especially from 10 a.m. – 2 p.m.
  - wear long-sleeve shirts, pants, hats, and sunglasses
- children under 6 months: Ask a doctor

Inactive ingredients

Purified Water, Cyclomethicone, C12-15 Alkyl Lactate, Butyloctyl Salicylate, Glyceryl Stearate SE, Isododecane, Glycerin, Cetearyl Alcohol, Butylene/Ethylene/Propylene Copolymer, Polyacrylamide, Cetyl Alcohol, Dicetyl Phosphate, Ceteth-10 Phosphate, Cholesterol, Tocopheryl Acetate, Edetate Disodium, Methylparaben, Phenoxyethanol, Xanthan Gum, Camellia Sinensis Leaf (Green Tea) Extract, Camellia Sinensis Leaf (White Tea) Extract, C13-C14 Isoparaffin, Laureth-7.

Other information

- protect product from excessive heat and direct sun

Questions or comments?

call 1-973-882-7512

Mfd. by: IGI Laboratories, Inc., Buena, NJ 08310

PRINCIPAL DISPLAY PANEL - 85 g Tube Carton

niseko®

SUNSCREEN

Broad Spectrum
SPF 25

UVA/UVB Protection

Formulated with
Green & White Tea • Vitamin E

Dermatologist-tested
Non-comedogenic

Net Wt. 3 oz (85 g)

MEDIMETRIKS
PHARMACEUTICALS, INC.